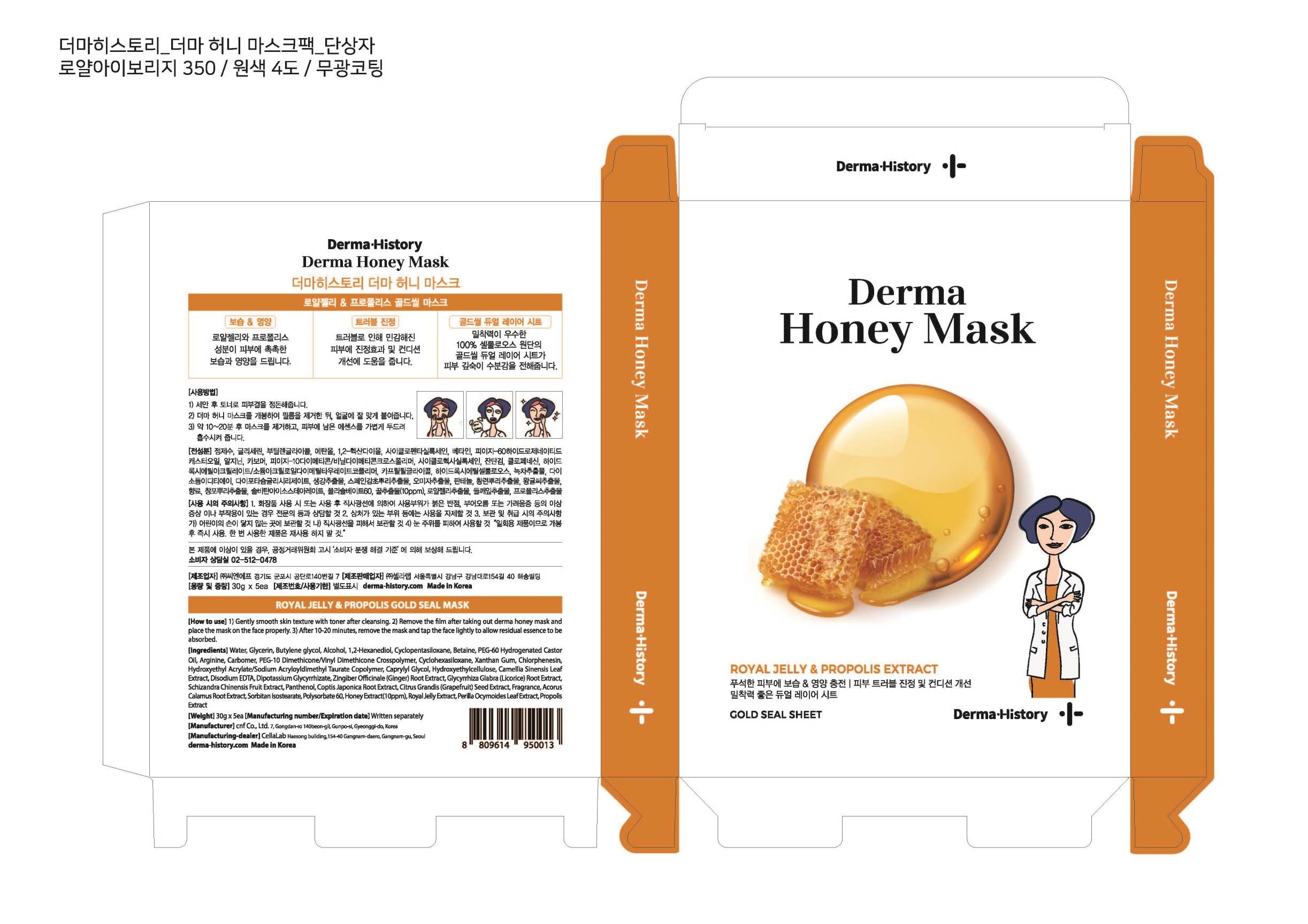 DRUG LABEL: Derma Honey Mask
NDC: 72312-0010 | Form: LIQUID
Manufacturer: CELLALAB
Category: otc | Type: HUMAN OTC DRUG LABEL
Date: 20180525

ACTIVE INGREDIENTS: GLYCERIN 2.53 g/100 g
INACTIVE INGREDIENTS: WATER; BUTYLENE GLYCOL

Drug Facts

ACTIVE INGREDIENT

Glycerin

INACTIVE INGREDIENT

Water, Butylene Glycol, etc.

PURPOSE

Skin Protectant - Skin Moisturizing & Nourishing / Soothing

keep out of reach of the children

INDICATIONS AND USAGE

1. Gently smooth skin texture with toner after cleansing.
2. Remove the film after taking out Derma Honey Mask and place the mask properly on face.
3. After 10-20 minutes, remove the mask and tap the face lightly to allow residual essence to be absorbed.

WARNINGS

1. Discontinue use and ask a doctor if any adverse reactions occur such as rash, swelling or irritation after use or due to direct sunlight.
2. Do not use on damaged or broken skin.
3. Storage and Handling Precautions

(A)Keep out of reach of children.

(B)Keep out of direct sunlight.

4. Avoid contact with eyes. "It is a disposable product and should be used immediately after opening. Do not reuse once-used products. "

DOSAGE AND ADMINISTRATION

for external use only